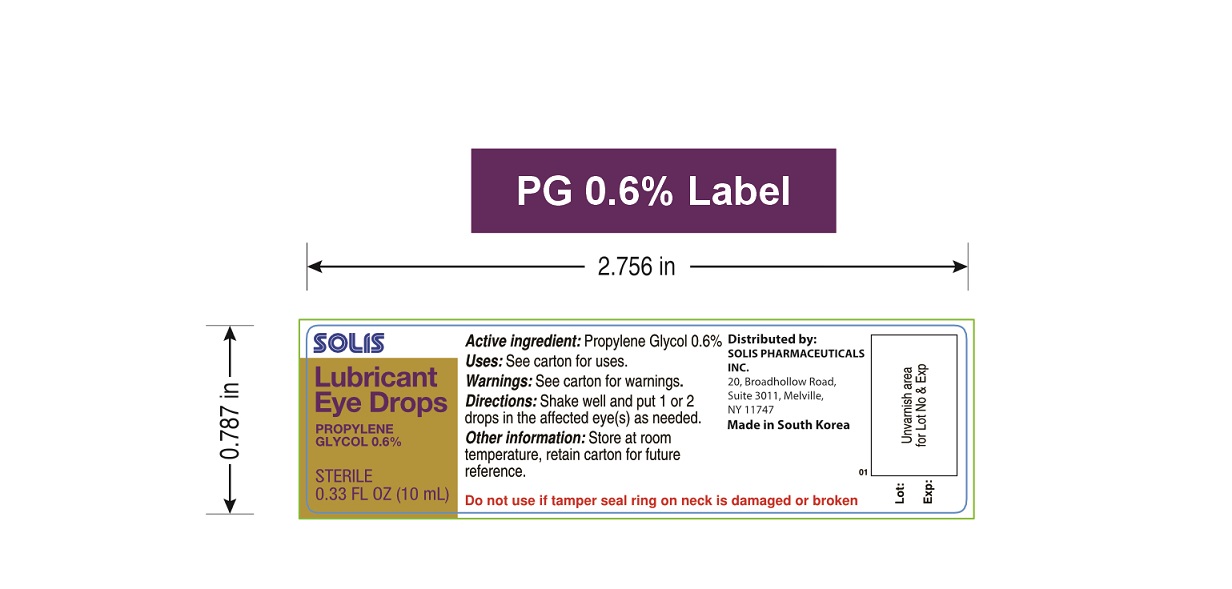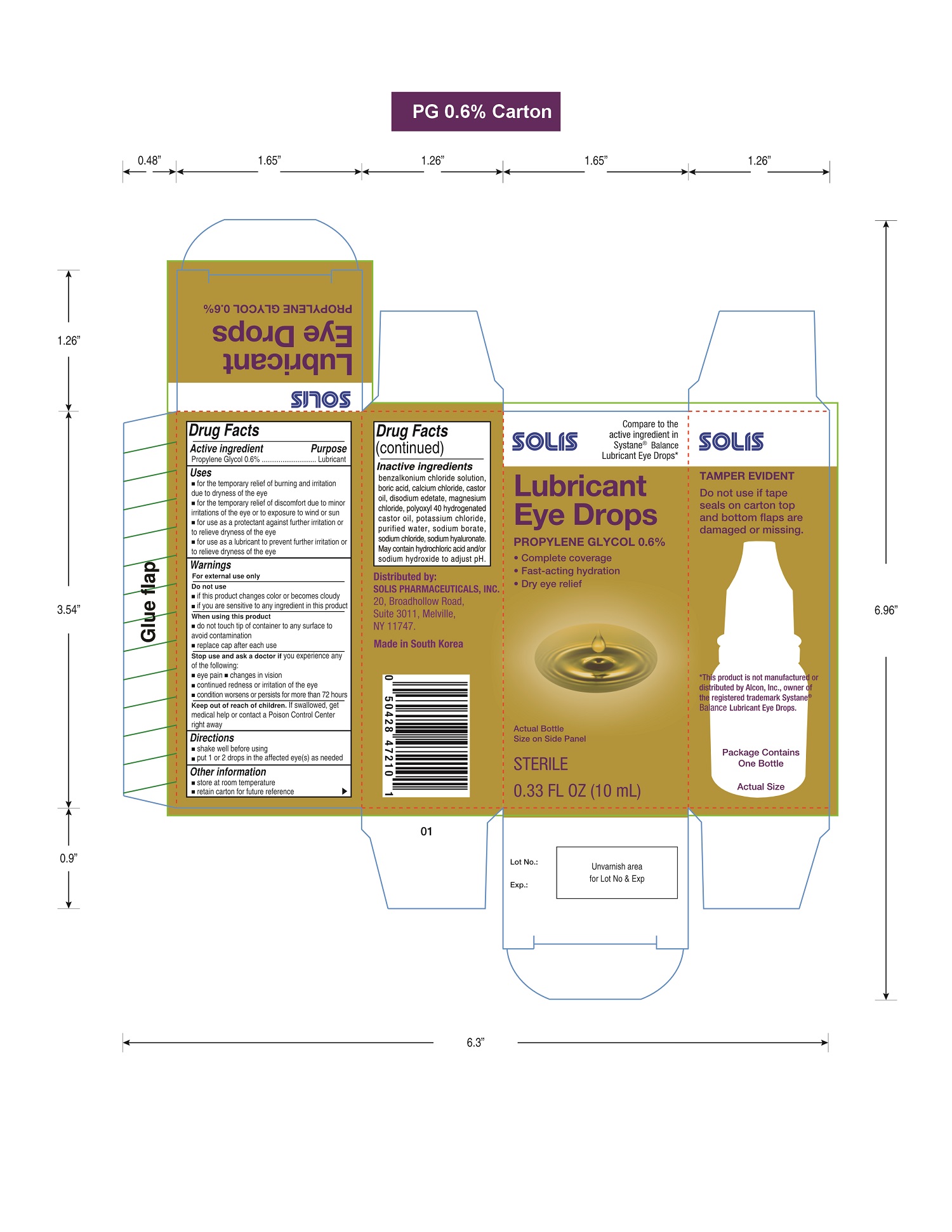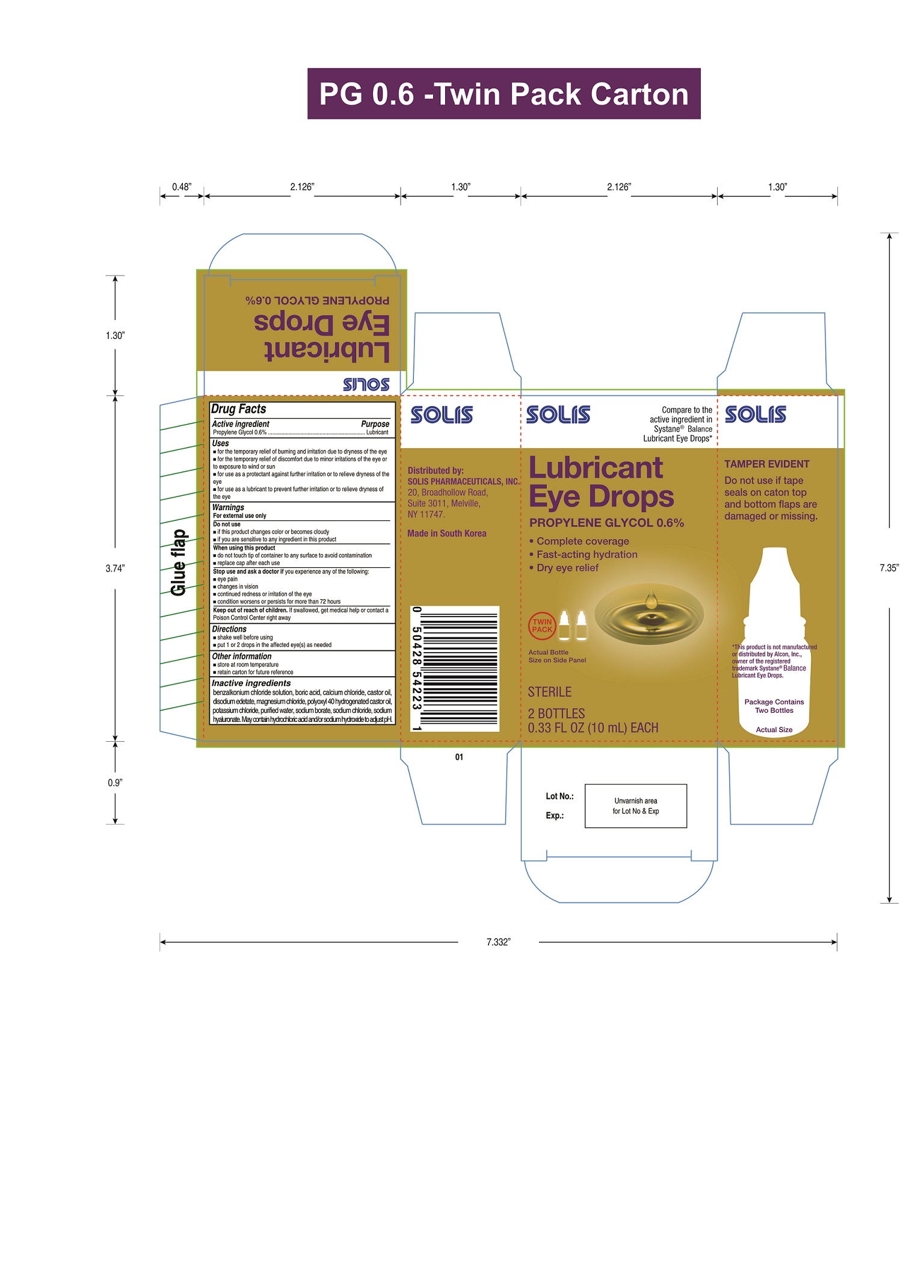 DRUG LABEL: Lubricant Eye Drops
NDC: 85185-002 | Form: SOLUTION/ DROPS
Manufacturer: Solis Pharmaceuticals Inc.
Category: otc | Type: HUMAN OTC DRUG LABEL
Date: 20250301

ACTIVE INGREDIENTS: PROPYLENE GLYCOL 6 mg/1 mL
INACTIVE INGREDIENTS: EDETATE DISODIUM; BORIC ACID; CALCIUM CHLORIDE; MAGNESIUM CHLORIDE; POTASSIUM CHLORIDE; WATER; SODIUM BORATE; SODIUM CHLORIDE; HYDROCHLORIC ACID; SODIUM HYDROXIDE; BENZALKONIUM CHLORIDE

Sterile Lubricant Eye Drops

Active ingredient

Propylene Glycol 0.6%

Purpose

Lubricant

Uses

- for the temporary relief of burning and irritation due to dryness of the eye
- for the temporary relief of discomfort due to minor irritations of the eye or to exposure to wind or sun
- for use as a protectant against further irritation or to relieve dryness of the eye
- for use as a lubricant to prevent further irritation or to relieve dryness of the eye

Warnings

- For external use only.
- Do not use
- if this product changes color or becomes cloudy
- if you are sensitive to any ingredient in this product
- When using this product
- do not touch tip of container to any surface to avoid contamination
- replace cap after each use

Stop use and ask a doctor if

you experience any of the following:

- eye pain,
- changes in vision,
- continued redness or irritation of the eye,
- condition worsens or persists for more than 72 hours.

Keep out of reach of children.

If swallowed, get medical help or contact a Poison Control Center right away.

Directions

- shake well before using
- Instill 1 or 2 drops in the affected eye(s) as needed.

Other information

- store at room temperature
- retain carton for future reference

Inactive ingredients

benzalkonium chloride solution, boric acid, calcium chloride, castor oil, disodium edetate, magnesium chloride, polyoxyl 40 hydrogenated castor oil, potassium chloride, purified water, sodium borate, sodium chloride, sodium hyaluronate. May contain hydrochloric acid and/or sodium hydroxide to adjust pH.